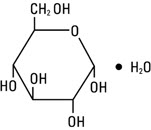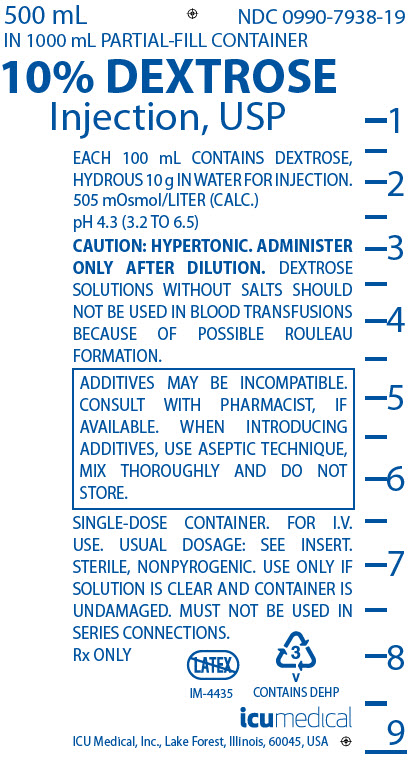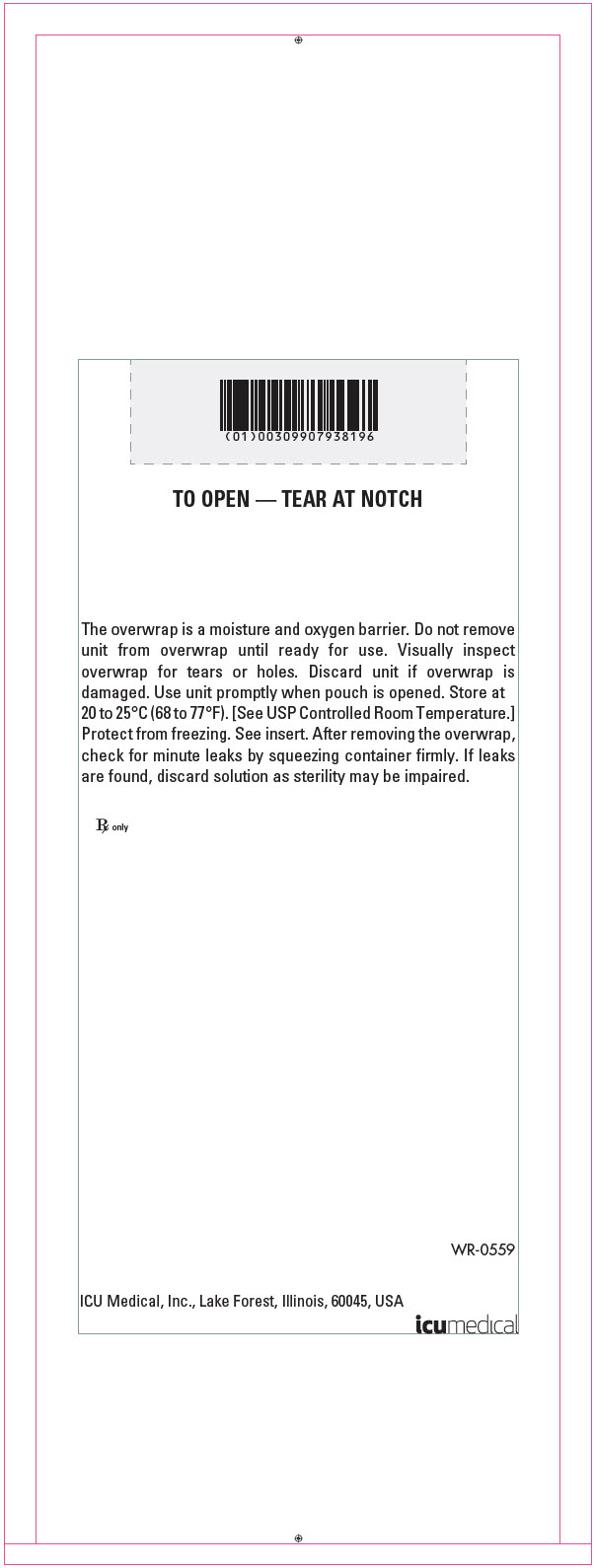 DRUG LABEL: Dextrose
NDC: 0990-7938 | Form: INJECTION, SOLUTION, CONCENTRATE
Manufacturer: ICU Medical, Inc.
Category: prescription | Type: HUMAN PRESCRIPTION DRUG LABEL
Date: 20251101

ACTIVE INGREDIENTS: DEXTROSE MONOHYDRATE 10 g/100 mL
INACTIVE INGREDIENTS: WATER

10% Dextrose Injection, USP
CONCENTRATED DEXTROSE IN WATER
Concentrated source of carbohydrate calories for intravenous infusion.
NOTE: This solution is hypertonic − see WARNINGS and PRECAUTIONS.
Partial-Fill Flexible Plastic Container Rx only

DESCRIPTION

10% Dextrose Injection, USP (concentrated dextrose in water) is a sterile, nonpyrogenic, hypertonic solution of Dextrose, USP in water for injection for intravenous administration after appropriate admixture or dilution.

10% Dextrose Injection, USP is provided as a 500 mL volume in a 1000 mL partial-fill container. The container is designed to facilitate admixture or dilution.

See table under HOW SUPPLIED for summary of content and characteristics of this concentrated solution.

The solution contains no bacteriostat, antimicrobial agent or added buffer and is intended only for use as a single-dose injection following admixture or dilution.

The flexible plastic container is fabricated from a specially formulated polyvinyl chloride. Water can permeate from inside the container into the overwrap but not in amounts sufficient to affect the solution significantly. Solutions in contact with the plastic container may leach out certain chemical components from the plastic in very small amounts; however, biological testing was supportive of the safety of the plastic container materials. Exposure to temperatures above 25°C/77°F during transport and storage will lead to minor losses in moisture content. Higher temperatures lead to greater losses. It is unlikely that these minor losses will lead to clinically significant changes within the expiration period.

Dextrose Injection, USP is a parenteral fluid and nutrient replenisher.

Dextrose Injection, USP is chemically designated D-glucose monohydrate (C6H12O6 • H2O), a hexose sugar freely soluble in water. It has the following structural formula:

Water for Injection, USP is chemically designated H2O.

CLINICAL PHARMACOLOGY

When administered intravenously, solutions containing carbohydrate in the form of dextrose restore blood glucose levels and provide calories. Carbohydrate in the form of dextrose may aid in minimizing liver glycogen depletion and exerts a protein sparing action. Dextrose Injection, USP undergoes oxidation to carbon dioxide and water.

Water is an essential constituent of all body tissues and accounts for approximately 70% of total body weight. Average normal adult daily requirement ranges from two to three liters (1.0 to 1.5 liters each for insensible water loss by perspiration and urine production, respectively).

Water balance is maintained by various regulatory mechanisms. Water distribution depends primarily on the concentration of electrolytes in the body compartments, and sodium (Na^+) plays a major role in maintaining physiologic equilibrium.

INDICATIONS AND USAGE

10% Dextrose Injection, USP (concentrated dextrose in water) in a partial-fill container is indicated for admixture with amino acids or dilution with other compatible IV fluids to provide a 5% final dextrose concentration for intravenous infusion in patients whose condition requires parenteral nutrition.

CONTRAINDICATIONS

A concentrated dextrose solution should not be used when intracranial or intraspinal hemorrhage is present nor in the presence of delirium tremens if the patient is already dehydrated.

Dextrose Injection, USP without electrolytes should not be administered simultaneously with blood through the same infusion set because of the possibility that pseudoagglutination of red cells may occur.

WARNINGS

Concentrated dextrose in water should be administered only after suitable dilution. Hypertonic dextrose solutions should be given slowly. Significant hyperglycemia and possible hyperosmolar syndrome may result from too rapid administration. The physician should be aware of the symptoms of hyperosmolar syndrome, such as mental confusion and loss of consciousness, especially in patients with chronic uremia and those with known carbohydrate intolerance.

The intravenous administration of this solution can cause fluid and/or solute overloading resulting in dilution of serum electrolyte concentrations, overhydration, congested states or pulmonary edema.

WARNING: This product contains aluminum that may be toxic. Aluminum may reach toxic levels with prolonged parenteral administration if kidney function is impaired. Premature neonates are particularly at risk because their kidneys are immature, and they require large amounts of calcium and phosphate solutions, which contain aluminum.

Research indicates that patients with impaired kidney function, including premature neonates, who receive parenteral levels of aluminum at greater than 4 to 5 mcg/kg/day accumulate aluminum at levels associated with central nervous system and bone toxicity. Tissue loading may occur at even lower rates of administration.

FOR PERIPHERAL VEIN ADMINISTRATION

Hypertonic dextrose solutions (above 5% concentration) should be given slowly, preferably through a small bore needle into a large vein, to minimize venous irritation.

FOR CENTRAL VENOUS ADMINISTRATION

Concentrated dextrose should be administered via central vein after appropriate admixture or dilution when required.

PRECAUTIONS

Electrolyte deficits, particularly in serum potassium and phosphate, may occur during prolonged use of concentrated dextrose solutions. Blood electrolyte monitoring is essential, and fluid and electrolyte imbalances should be corrected. Essential vitamins and minerals also should be provided as needed.

Solutions containing dextrose should be used with caution in patients with known subclinical or overt diabetes mellitus.

Care should be exercised to insure that the needle (or catheter) is well within the lumen of the vein and that extravasation does not occur.

Concentrated dextrose solutions should not be administered subcutaneously or intramuscularly.

Do not administer unless solution is clear and container is undamaged. Discard unused portion.

PREGNANCY

Pregnancy Category C. Animal reproduction studies have not been conducted with dextrose. It is also not known whether dextrose can cause fetal harm when administered to a pregnant woman or can affect reproduction capacity. Dextrose should be given to a pregnant woman only if clearly needed.

This product contains no more than 25 mcg/L of aluminum.

ADVERSE REACTIONS

Hyperosmolar syndrome, resulting from excessively rapid administration of concentrated dextrose may cause hypovolemia, dehydration, mental confusion and/or loss of consciousness.

Reactions which may occur because of the solution or the technique of administration include febrile response, infection at the site of injection, venous thrombosis or phlebitis extending from the site of injection, extravasation and hypervolemia.

If an adverse reaction does occur, discontinue the infusion, evaluate the patient, institute appropriate therapeutic countermeasures and save the remainder of the fluid for examination if deemed necessary.

OVERDOSAGE

In the event of overhydration or solute overload during therapy, re-evaluate the patient and institute appropriate corrective measures. (See WARNINGS and PRECAUTIONS).

DOSAGE AND ADMINISTRATION

Concentrated Dextrose in Water is administered by slow intravenous infusion (a) after admixture with amino acid solutions or (b) after dilution with other compatible IV fluids. Dosage should be adjusted to meet the requirements of each individual patient.

The maximum rate at which dextrose can be infused without producing glycosuria is 0.5 g/kg of body weight /hr. About 95% of the dextrose is retained when infused at a rate of 0.8 g/kg/hr.

Clinical evaluation and periodic laboratory determinations are necessary to monitor changes in fluid balance, electrolyte concentrations, and acid-base balance during prolonged parenteral therapy or whenever the condition of the patient warrants such evaluation.

A list of nutritional admixture values is appended.

Parenteral drug products should be inspected visually for particulate matter and discoloration prior to administration, whenever solution and container permit. (See PRECAUTIONS).

Drug Interaction

Additives may be incompatible. Consult with pharmacist, if available. When introducing additives, use aseptic technique, mix thoroughly and do not store.

Some opacity of the plastic due to moisture absorption during sterilization process may be observed. This is normal and does not affect the solution quality or safety. The opacity will diminish gradually.

WARNING: Do not use flexible container in series connections.

HOW SUPPLIED

10% Dextrose Injection, USP is supplied in single-dose, partial-fill, flexible containers as follows: a 500 mL volume in a 1000 mL container. See the following table.

Concentrated Dextrose In Water Content and Characteristics
NDC No. | % Conc. | Fill Volume (mL) | Total Grams of Dextrose Hydrous Per Container | kcal [Caloric value calculated on the basis of 3.4 kcal/g of dextrose, hydrous.] /100 mL; (Per Container) | mOsmol/liter; (calc.) | pH (range)
0409-7938-19 | 10 | 500 | 50 | 34 (170) | 505 | 4.3 (3.2 to 6.5)
0990-7938-19 | 10 | 500 | 50 | 34 (170) | 505 | 4.3 (3.2 to 6.5)

ICU Medical is transitioning NDC codes from the "0409" to a "0990" labeler code. Both NDC codes are expected to be in the market for a period of time.

Nutritional Admixture Values Equal volumes of 10% Dextrose Injection, USP and Aminosyn™ 7% provide the following:
Dextrose; Pre-Dilution Concentration | Admixture; Non-Protein kcal/g N | Admixture; Non-Protein; kcal/liter | Admixture; g N/liter | Admixture Dextrose Concentration
10% | 31 | 170 | 5.5 | 5%

Store at 20 to 25°C (68 to 77°F). [See USP Controlled Room Temperature.] Protect from freezing.

Revised: November, 2018

EN-4694

ICU Medical, Inc., Lake Forest, Illinois, 60045, USA

PRINCIPAL DISPLAY PANEL - 500 mL Bag Label

500 mL
NDC 0990-7938-19
IN 1000 mL PARTIAL-FILL CONTAINER
10% DEXTROSE
Injection, USP

EACH 100 mL CONTAINS DEXTROSE,
HYDROUS 10 g IN WATER FOR
INJECTION.
505 mOsmol/LITER (CALC.)
pH 4.3 (3.2 TO 6.5)

CAUTION: HYPERTONIC. ADMINISTER
ONLY AFTER DILUTION. DEXTROSE
SOLUTIONS WITHOUT SALTS
SHOULD NOT BE USED IN BLOOD
TRANSFUSIONS BECAUSE OF
POSSIBLE ROULEAU FORMATION.

ADDITIVES MAY BE
INCOMPATIBLE. CONSULT WITH
PHARMACIST, IF AVAILABLE.
WHEN INTRODUCING ADDITIVES,
USE ASEPTIC TECHNIQUE, MIX
THOROUGHLY AND DO NOT
STORE.

SINGLE-DOSE CONTAINER. FOR I.V.
USE. USUAL DOSAGE: SEE INSERT.
STERILE, NONPYROGENIC. USE ONLY
IF SOLUTION IS CLEAR AND
CONTAINER IS UNDAMAGED.
MUST NOT BE USED IN SERIES
CONNECTIONS.

Rx ONLY
IM-4435
3
V
CONTAINS DEHP

icumedical

ICU Medical, Inc., Lake Forest, Illinois, 60045 USA

PRINCIPAL DISPLAY PANEL - 500 mL Bag Pouch Label

TO OPEN — TEAR AT NOTCH

The overwrap is a moisture and oxygen barrier. Do not remove
unit from overwrap until ready for use. Visually inspect
overwrap for tears or holes. Discard unit if overwrap is
damaged. Use unit promptly when pouch is opened.
Store at 20 to 25°C (68 to 77°F). [See USP Controlled Room
Temperature.] Protect from freezing. See insert. After removing
the overwrap, check for minute leaks by squeezing container
firmly. If leaks are found, discard solution as sterility may be
impaired.

Rx only

WR-0559

ICU Medical, Inc., Lake Forest, Illinois, 60045 USA

icumedical